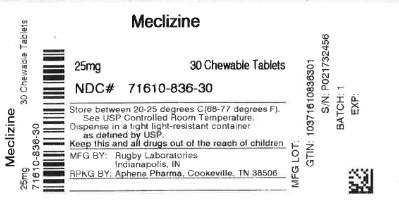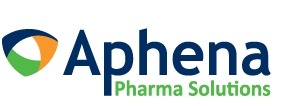 DRUG LABEL: Meclizine Hydrochloride
NDC: 71610-836 | Form: TABLET, CHEWABLE
Manufacturer: Aphena Pharma Solutions - Tennessee, LLC		
Category: otc | Type: HUMAN OTC DRUG LABEL
Date: 20240610

ACTIVE INGREDIENTS: MECLIZINE HYDROCHLORIDE 25 mg/1 1
INACTIVE INGREDIENTS: CROSPOVIDONE; VANILLA; MAGNESIUM STEARATE; RASPBERRY; STEARIC ACID; SILICON DIOXIDE; FD&C RED NO. 40; LACTOSE MONOHYDRATE; SACCHARIN SODIUM; CROSCARMELLOSE SODIUM

5172C- Rubgy

Drug Facts

Active ingredient (in each chewable tablet)
Meclizine HCl 25 mg

Purpose
Antiemetic

Uses

prevents and treats nausea, vomiting or dizziness due to motion sickness

WARNINGS

Do not use in

children under 12 years of age unless directed by a doctor

Ask a doctor before use if you have

 glaucoma

 a breathing problem such as emphysema or chronic bronchitis
 trouble urinating due to an enlarged prostate gland

Ask a doctor or pharmacist before use if

you are taking sedatives or tranquilizers

When using this product

 Do not exceed recommended dosage

 may cause drowsiness

 alcohol, sedatives, and tranquilizers may increase drowsiness

 avoid alcoholic drinks
 use caution when driving a motor vehicle or operating machinery

PREGNANCY OR BREAST FEEDING

If pregnant or breast-feeding,ask a health professional before use.

Keep out of reach of children.

OVERDOSAGE

In case of overdose, get medical help or contact a Poison Control Center right away (1-800-222-1222).

Directions

 Dosage should be taken one hour before travel starts

adults and children 12 years of age and over | chew 1 to 2 tablets once daily, or as directed by a doctor
children under 12 years of age | do not give this product to children under 12 years of age unless directed by a doctor

Other information

 Store in a dry place at 15°-30°C (59°-86°F)
 keep lid tightly closed

INACTIVE INGREDIENT

Croscarmellose Sodium, Crospovidone, FD&C Red #40 Lake, French Vanilla Flavor, Lactose, Magnesium Stearate, Raspberry Flavor, Silica, Sodium Saccharin, Stearic Acid

Questions or comments?

1-800-645-2158

TAMPER EVIDENT: DO NOT USE IF IMPRINTED SAFETY SEAL UNDER CAP IS BROKEN OR MISSING

*This product is not manufactured or distributed by Wellspring Pharmaceutical Corporation, owner of the registered trademark Bonine®.

Distributed by:
RUGBY® LABORATORIES
Indianapolis, IN 46268
www.rugbylaboratories.com

REPACKAGING INFORMATION

Please reference the HOW SUPPLIED section listed above for a description of individual drug products listed below. This drug product has been received by Aphena Pharma Solutions - Tennessee, LLC in a manufacturer or distributor packaged configuration and repackaged in full compliance with all applicable cGMP regulations. The package configurations available from Aphena are listed below:

25mg
NDC 71610-836-30, Bottles of 30 Tablets
NDC 71610-836-53, Bottles of 60 Tablets
NDC 71610-836-60, Bottles of 90 Tablets
NDC 71610-836-80, Bottles of 180 Tablets

Store between 20°-25°C (68°-77°F). See USP Controlled Room Temperature. Dispense in a tight light-resistant container as defined by USP. Keep this and all drugs out of the reach of children.
Repackaged by:

Cookeville, TN 38506

20240529AMH

PRINCIPAL DISPLAY PANEL - 25mg

NDC 71610-836 - Meclizine 25mg Tablets - Rx Only